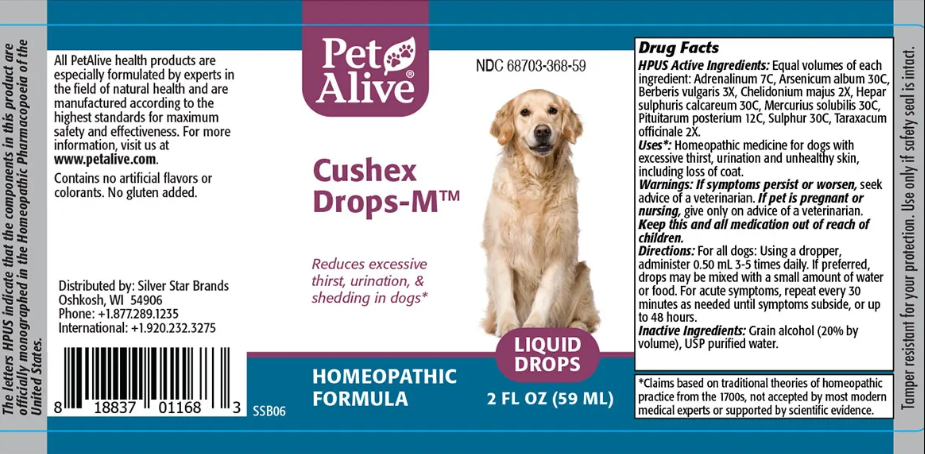 DRUG LABEL: PetAlive Cushex Drops-M
NDC: 68703-368 | Form: TINCTURE
Manufacturer: SILVER STAR BRANDS
Category: homeopathic | Type: OTC ANIMAL DRUG LABEL
Date: 20251216

ACTIVE INGREDIENTS: EPINEPHRINE 7 [hp_C]/1 mL; ARSENIC TRIOXIDE 30 [hp_C]/1 mL; BERBERIS VULGARIS ROOT BARK 3 [hp_X]/1 mL; CHELIDONIUM MAJUS 2 [hp_X]/1 mL; CALCIUM SULFIDE 30 [hp_C]/1 mL; MERCURIUS SOLUBILIS 30 [hp_C]/1 mL; SUS SCROFA PITUITARY GLAND, POSTERIOR 12 [hp_C]/1 mL; SULFUR 30 [hp_C]/1 mL; TARAXACUM OFFICINALE 2 [hp_X]/1 mL
INACTIVE INGREDIENTS: ALCOHOL; WATER

Cushex Drops-M

PURPOSE

Reduce excessive thirst, urination and shedding in dogs

HPUS Active Ingredients: Equal volumes of each ingredient:

Adrenalinum 7C

Arsenicum album 30C

Berberis vulgaris 3X

Chelidonium majus 2X

Hepar sulphuris calcareum 30C

Mercurius solubilis 30C

Pituitarum posterium 12C

Sulphur 30C

Taraxacum officinale 2X

INDICATIONS AND USAGE

Uses: Homeopathic medicine for dogs with excessive thirst, urination and unhealthy skin, including loss of coat

WARNINGS

Warnings: If symptoms persist or worsen, seek advice of a veterinarian

PREGNANCY OR BREAST FEEDING

If pet is pregnant or nursing, give only on advice of a veterinarian.

KEEP OUT OF REACH OF CHILDREN

Keep this and all medication out of reach of children.

DOSAGE AND ADMINISTRATION

Directions: For all dogs: Using a dropper, administer 0.50 mL 3-5 times daily. If preferred, drops may be mixed with a small amount of water or food. For acute symptoms, repeat every 30 minutes as needed until symptoms subside, or up to 48 hours.

INACTIVE INGREDIENT

Inactive Ingredients: Grain alcohol (20% by volume), USP purified water

INFORMATION FOR OWNERS/CAREGIVERS

The letters HPUS indicate that the components in this product are officially monographed in the Homeopathic Pharmacopoeia of the United States

All PetAlive health products are especially formulated by experts in the field of natural health and are manufactured according to the highest standards for maximum safety and effectiveness. For more information, visit us at www.petalive.com.

Contains no artificial flavors or colorants. No gluten added.

Distributed by: Silver Star Brands
Oshkosh, WI 54906
Phone: +1.877.289.1235
International: +1.920.232.3275

STORAGE AND HANDLING

Tamper resistant for your protection, Use only if safety seal is intact